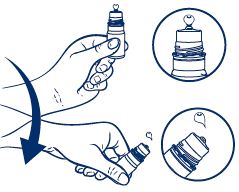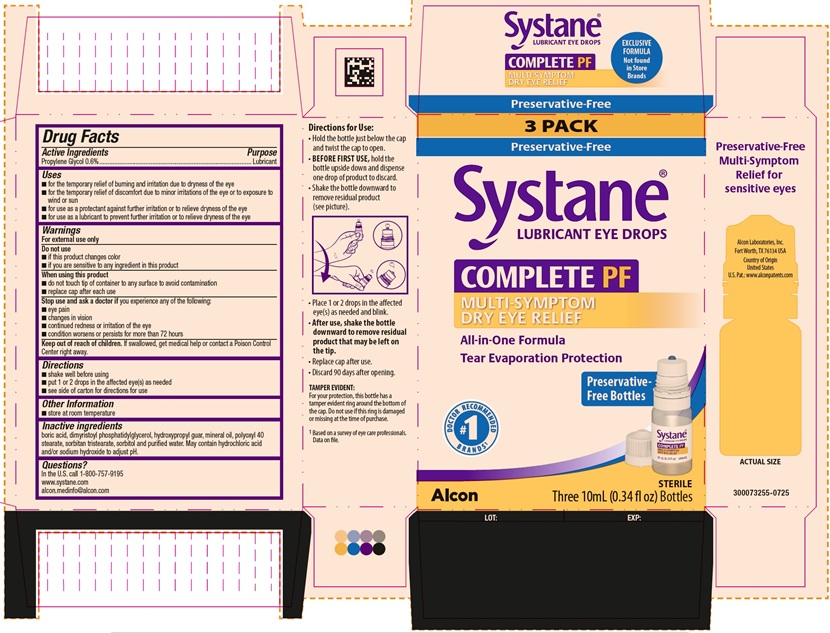 DRUG LABEL: Systane Complete PF
NDC: 0065-2509 | Form: EMULSION
Manufacturer: Alcon Laboratories, Inc.
Category: otc | Type: HUMAN OTC DRUG LABEL
Date: 20251103

ACTIVE INGREDIENTS: Propylene Glycol .06 mg/1 mL
INACTIVE INGREDIENTS: Boric Acid; Dimyristoylphosphatidylglycerol, Dl-; Guaraprolose (3500 Mpa.S At 1%); Mineral Oil; Polyoxyl 40 Stearate Type I; Sorbitan Tristearate; Sorbitol; Water; Hydrochloric Acid; Sodium Hydroxide

Drug Facts

ACTIVE INGREDIENT

Active Ingredients | Purpose
Propylene Glycol 0.06% | Lubricant

Uses

- for the temporary relief of burning and irritation due to dryness of the eye
- for the temporary relief of discomfort due to minor irritations of the eye or to exposure to wind or sun
- for use as a protectant against further irritation or to relieve dryness of the eye
- for use as a lubricant to prevent further irritation or to relieve dryness of the eye

Warnings

For external use only

Do not use

- if this product changes color
- if you are sensitive to any ingredient in this product

When using this product

- do not touch tip of container to any surface to avoid contamination
- replace cap after each use

Stop use and ask a doctor if you experience any of the following:

- eye pain
- changes in vision
- continued redness or irritation of the eye
- condition worsens or persists for more than 72 hours

Keep out of reach of children.

If swallowed, get medical help or contact a Poison Control Center right away.

Directions

- shake well before using
- put 1 or 2 drops in the affected eye(s) as needed
- see side of carton for directions for use

Other information

- store at room temperature

Inactive ingredients

boric acid, dimyristoyl phosphatidylglycerol, hydroxypropyl guar, mineral oil, polyoxyl 40 stearate, sorbitan tristearate, sorbitol and purified water. May contain hydrochloric acid and/or sodium hydroxide to adjust pH.

Questions?

In the U.S. call 1-800-757-9195
www.systane.com
alcon.medinfo@alcon.com

Directions for Use:

- Hold the bottle just below the cap and twist the cap to open.
- BEFORE FIRST USE, hold the bottle upside down and dispense one drop of product to discard.
- Shake the bottle downward to remove residual product (see picture).

- Place 1 or 2 drops in the affected eye(s) as needed and blink.
- After use, shake the bottle downward to remove residual product that may be left on the tip.
- Replace cap after use.
- Discard 90 days after opening.

TAMPER EVIDENT:
For your protection, this bottle has a tamper evident ring around the bottom of the cap. Do not use if this ring is damaged or missing at the time of purchase.

^1Based on a survey of eye care professionals. Data on file.

PRINCIPAL DISPLAY PANEL

3 PACK
Preservative-Free
SYSTANE® LUBRICANT EYE DROPS
COMPLETE PF
MULTI-SYMPTON
DRY EYE RELIEF
All-in-One Formula
Tear evaporation protection
Preservative-Free Bottles
#1 Doctor Recommended Brands^1
Alcon
Sterile
Three 10mL (0.34 FL OZ) Bottles
LOT: EXP:
Side Panel:
Preservative-Free
Multi-Symptom
Relief for
Sensitive eyes
Alcon Laboratories, Inc.
Fort Worth, TX 76134 USA
Country of Origin: United States
U.S. Patent: www.alconpatents.com
Actual Size
300073255-0725